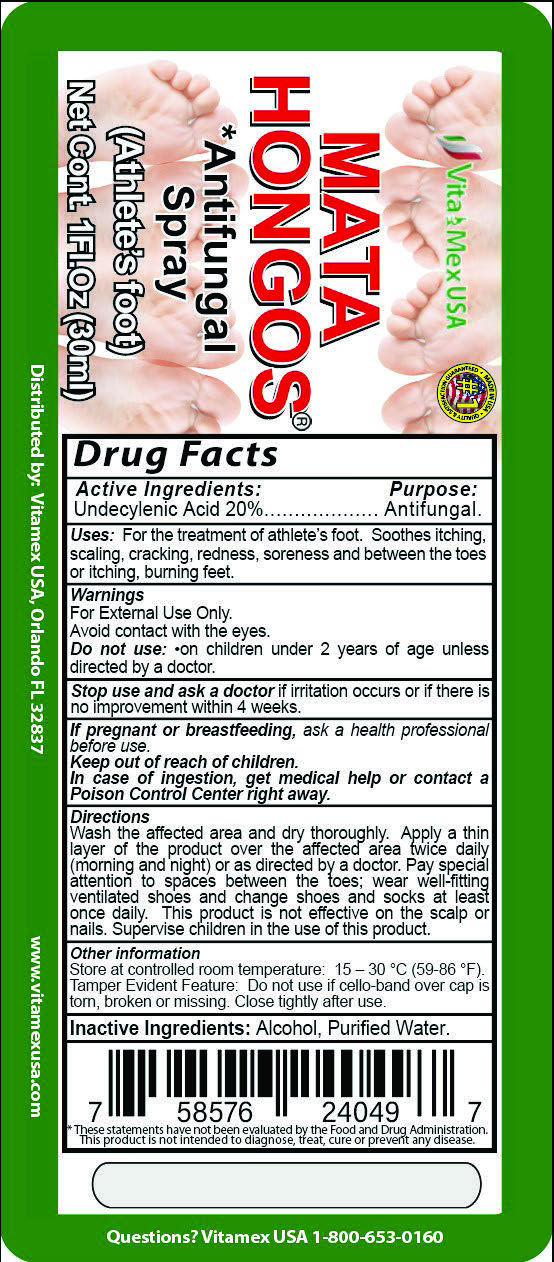 DRUG LABEL: Mata Hongos
NDC: 69469-201 | Form: SPRAY
Manufacturer: Vitamex USA, Corp
Category: otc | Type: HUMAN OTC DRUG LABEL
Date: 20250123

ACTIVE INGREDIENTS: UNDECYLENIC ACID 2 mg/10 mL
INACTIVE INGREDIENTS: ALCOHOL; WATER

Mata Hongos 1oz

Active Ingredient

Active Ingredient: Purpose:

Undecylenic Acid 20% Antifungal

PURPOSE

Uses: For the treament of athlete's foot. Soothes itching, scailing, cracking, redness, soreness and between the toes or itching, burning feet.

Warnings

For External Use Only

Avoid contact with the eyes.

Do not use: on children under 2 years of age unless directed by doctor.

Stop use and ask a doctor: if irritation occurs or if there is no improvement within 4 weeks.

If pregnant or breastfeeding, ask health professional before use.

Keep out or reach of children

In case of ingestion, get medical help or contct a Poison Control Center right away.

Keep out of reach of children

If pregnant or breastfeeding, ask health professional before use.

Keep out or reach of children

In case of ingestion, get medical help or contct a Poison Control Center right away.

Directions

Wash the affected area and dry throughly. Apply a thin layer of the product over the affected area twice daily (morning and night) or as directed by a doctor. Pay special attention to spaces between the toes; wear well-fitting ventialted shoes and change shoes and socks at least once daily. This product is not effective on the scalp or nails. Supervise children in the use of this product.

Directions

Wash the affected area and dry throughly. Apply a thin layer of the product over the affected area twice daily (morning and night) or as directed by a doctor. Pay special attention to spaces between the toes; wear well-fitting ventialted shoes and change shoes and socks at least once daily. This product is not effective on the scalp or nails. Supervise children in the use of this product.

Other Information

Store at controlled room temperature: 15-30°C (59-86°F) Tamper Evident Feature: Do not use cello-band over cap is torn, broken or missing. Close tightly after use.

Inactive Ingredients

Inactive Ingredientes: Alcohol, Purified Water

Mata Hongos

Antifungal spray

(Athlete's Foot)

Net Cont. 1 Fl. Oz (30mL)